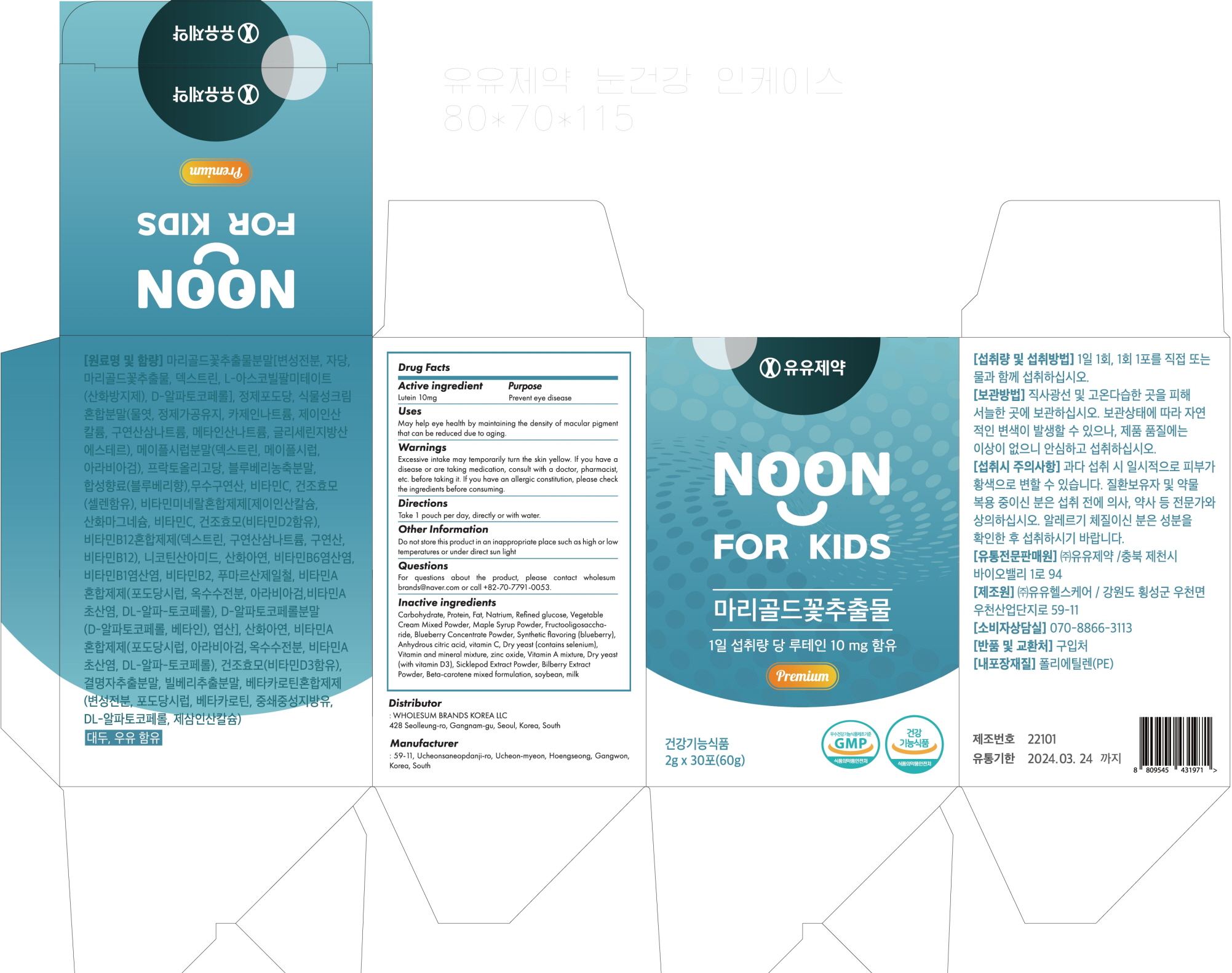 DRUG LABEL: Noon for Kids
NDC: 82597-010 | Form: POWDER
Manufacturer: Wholesum Brands Co., Ltd.
Category: otc | Type: HUMAN OTC DRUG LABEL
Date: 20240124

ACTIVE INGREDIENTS: Lutein 10 mg/2 g
INACTIVE INGREDIENTS: Blueberry; ASCORBIC ACID

ACTIVE INGREDIENT

Lutein 10mg

INACTIVE INGREDIENTS

Carbohydrate, Protein, Fat, Natrium, Refined glucose, Vegetable Cream Mixed Powder, Maple Syrup Powder, Fructooligosaccharide, Blueberry Concentrate Powder, Synthetic flavoring (blueberry), Anhydrous citric acid, vitamin C, Dry yeast (contains selenium), Vitamin and mineral mixture, zinc oxide, Vitamin A mixture, Dry yeast (with vitamin D3), Sicklepod Extract Powder, Bilberry Extract Powder, Beta-carotene mixed formulation, soybean, milk

PURPOSE

Prevent eye diseases

WARNINGS

Excessive intake may temporarily turn the skin yellow. If you have a disease or are taking medication, consult with a doctor, pharmacist, etc. before taking it. If you have an allergic constitution, please check the ingredients before consuming.

KEEP OUT OF REACH OF CHILDREN

Not Applicable

Uses

May help eye health by maintaining the density of macular pigment that can be reduced due to aging.

Directions

Take 1 pouch per day, directly or with water.

Other Information

Do not store this product in an inappropriate place such as high or low temperatures or under direct sun light

Questions

For questions about the product, please contact wholesumbrands@naver.com or call +82-70-7791-0053.